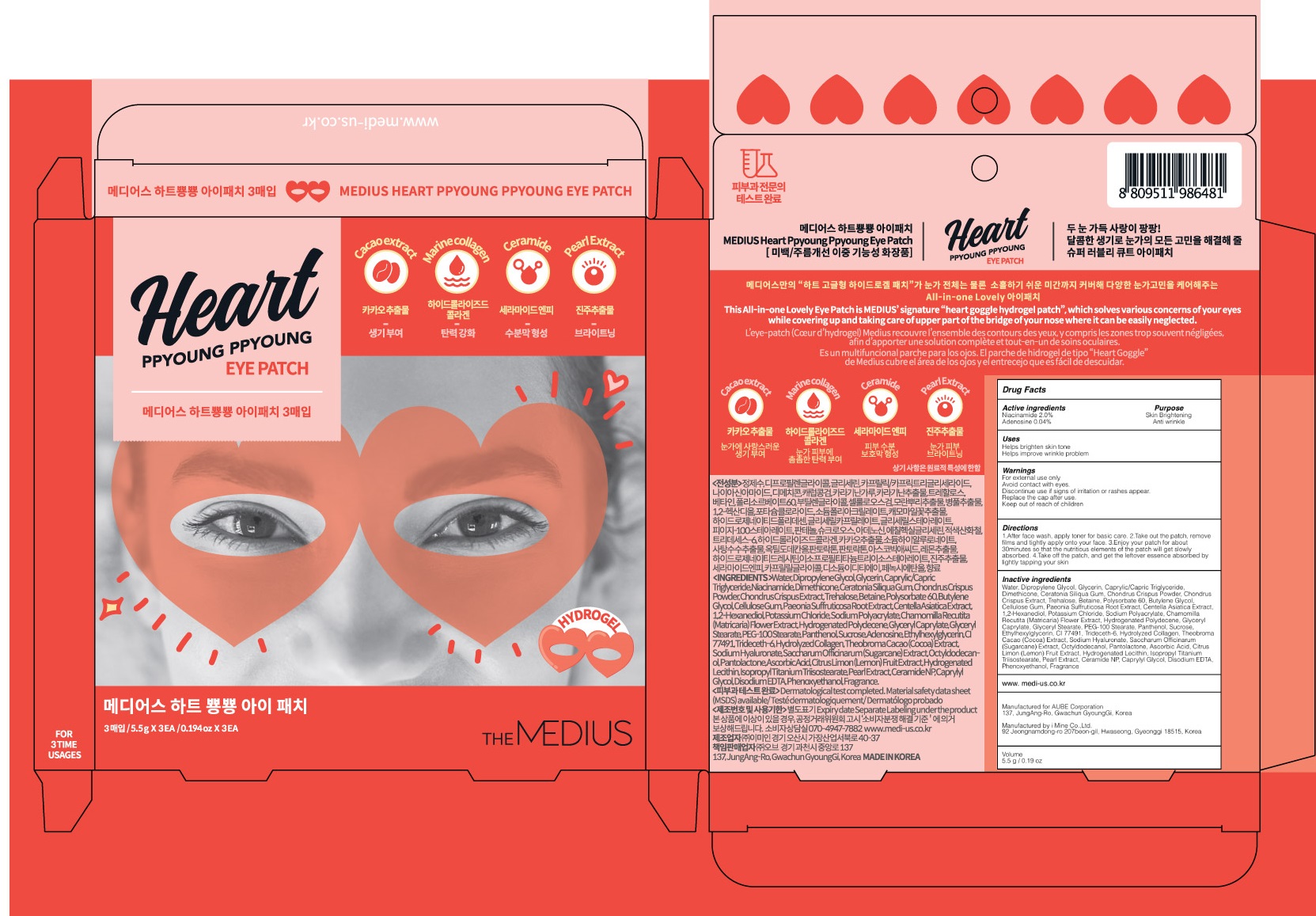 DRUG LABEL: MEDIUS Heart Ppyoung Ppyoung Eye
NDC: 72868-010 | Form: PATCH
Manufacturer: Aube. Corporation
Category: otc | Type: HUMAN OTC DRUG LABEL
Date: 20190215

ACTIVE INGREDIENTS: Niacinamide 0.11 g/5.5 g; Adenosine 0.002 g/5.5 g
INACTIVE INGREDIENTS: Water; Dipropylene Glycol

ACTIVE INGREDIENT

Active Ingredients: Niacinamide 2.0%, Adenosine 0.04%

INACTIVE INGREDIENT

Inactive ingredients:
Water, Dipropylene Glycol, Glycerin, Caprylic/Capric Triglyceride, Dimethicone, Ceratonia Siliqua Gum, Chondrus Crispus Powder, Chondrus Crispus Extract, Trehalose, Betaine, Polysorbate 60, Butylene Glycol, Cellulose Gum, Paeonia Suffruticosa Root Extract, Centella Asiatica Extract, 1,2-Hexanediol, Potassium Chloride, Sodium Polyacrylate, Chamomilla Recutita (Matricaria) Flower Extract, Hydrogenated Polydecene, Glyceryl Caprylate, Glyceryl Stearate, PEG-100 Stearate, Panthenol, Sucrose, Ethylhexylglycerin, CI 77491, Trideceth-6, Hydrolyzed Collagen, Theobroma Cacao (Cocoa) Extract, Sodium Hyaluronate, Saccharum Officinarum (Sugarcane) Extract, Octyldodecanol, Pantolactone, Ascorbic Acid, Citrus Limon (Lemon) Fruit Extract, Hydrogenated Lecithin, Isopropyl Titanium Triisostearate, Pearl Extract, Ceramide NP, Caprylyl Glycol, Disodium EDTA, Phenoxyethanol, Fragrance

PURPOSE

Purpose: Skin Brightening, Anti wrinkle

WARNINGS

For external use only
Avoid contact with eyes.
Discontinue use if signs of irritation or rashes appear.
Replace the cap after use.
Keep out of reach of children

KEEP OUT OF REACH OF CHILDREN

Uses

Helps brighten skin tone
Helps improve wrinkle problem

Directions

1.After face wash, apply toner for basic care.

2.Take out the patch, remove films and tightly apply onto your face.

3.Enjoy your patch for about 30minutes so that the nutritious elements of the patch will get slowly absorbed.

4.Take off the patch, and get the leftover essence absorbed by lightly tapping your skin